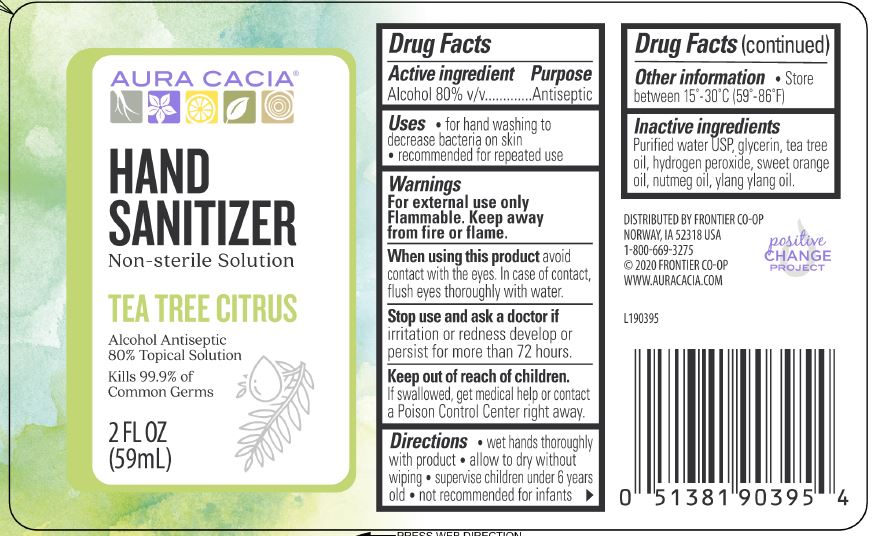 DRUG LABEL: Aura Cacia Hand Sanitizer
NDC: 74246-103 | Form: SOLUTION
Manufacturer: Frontier Co-op
Category: otc | Type: HUMAN OTC DRUG LABEL
Date: 20231220

ACTIVE INGREDIENTS: ALCOHOL 80 mL/100 mL
INACTIVE INGREDIENTS: TEA TREE OIL; NUTMEG OIL; ORANGE OIL; CANANGA OIL; GLYCERIN; WATER; HYDROGEN PEROXIDE

Aura Cacia Hand Sanitizer Tea Tree Citrus

Drug Facts

Active ingredient

Alcohol 80% v/v

Purpose

Antiseptic

Uses

- for hand washing to decrease bacteria on the skin
- recommended for repeated use

Warnings

For external use only

Flammable. Keep away from fire or flame.

When using this product avoid contact with the eyes. In case of contact, flush eyes thoroughly with water.

Stop use and ask a doctor if irritation or redness develop or persist for more than 72 hours.

Keep out of reach of children. If swallowed, get medical help or contact a Poison Control Center right away.

Directions

- wet hands thoroughly with product
- allow to dry without wiping
- supervise children under 6 years old
- not recommended for infants

Other information

- Store between 15°-30°C (59°-86°F)

Inactive ingredients

Purified water USP, glycerin, tea tree oil, hydrogen peroxide, sweet orange oil, nutmeg oil, ylang ylang oil.

DISTRIBUTED BY FRONTIER CO-OP

NORWAY, IA 52318 USA

1-800-669-3275

©2020 FRONTIER CO-OP

WWW.AURACACIA.COM

PACKAGE LABEL

AURA CACIA®

HAND SANITIZER

Non-sterile Solution

TEA TREE CITRUS

Alcohol Antiseptic 80% Topical Solution

Kills 99.9% of Common Germs

2 FL OZ (59 mL)